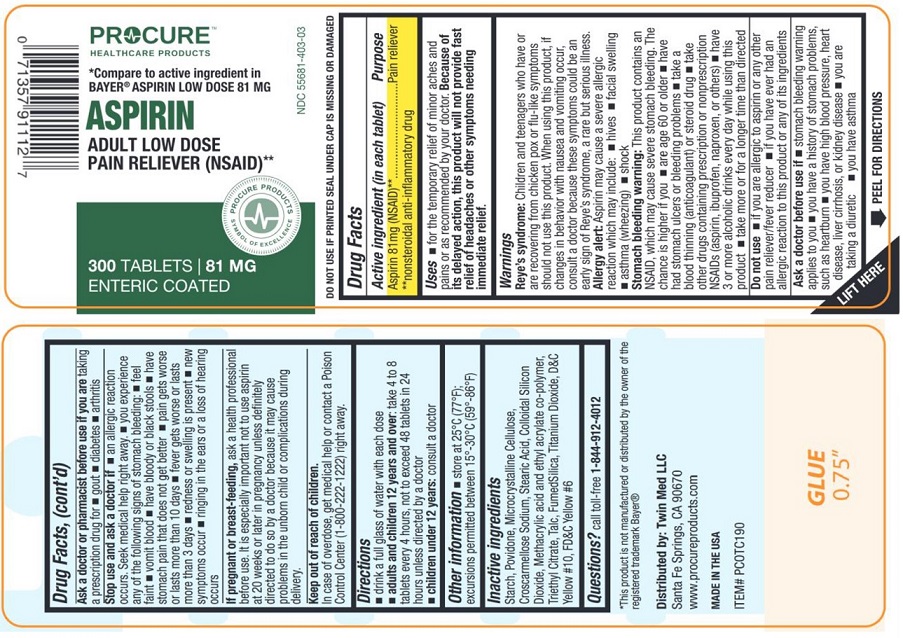 DRUG LABEL: Adult Low Dose Pain Reliever
NDC: 55681-403 | Form: TABLET, DELAYED RELEASE
Manufacturer: TWIN MED LLC
Category: otc | Type: HUMAN OTC DRUG LABEL
Date: 20250703

ACTIVE INGREDIENTS: ASPIRIN 81 mg/1 1
INACTIVE INGREDIENTS: STARCH, CORN; POVIDONE; MICROCRYSTALLINE CELLULOSE; CROSCARMELLOSE SODIUM; STEARIC ACID; SILICON DIOXIDE; METHACRYLIC ACID AND ETHYL ACRYLATE COPOLYMER; TRIETHYL CITRATE; TALC; TITANIUM DIOXIDE; D&C YELLOW NO. 10; FD&C YELLOW NO. 6

Adult Low Dose Aspirin Delayed Release Tablets, 81 mg

Drug Facts

Active ingredients (in each tablet)

Aspirin 81 mg (NSAID)**

**nonsteroidal anti-inflammatory drug

Purpose

Pain reliever

Uses

- for the temporary relief of minor aches and pains or as recommended by your doctor. Because of its delayed action, this product will not provide fast relief of headaches or symptoms needing immediate relief.

Warnings

Reye's syndrome:Children and teenagers who have or are recovering from chicken pox or flu-like symptoms should not use this product. When using this product, if changes in behavior with nausea and vomiting occur, consult a doctor because these symptoms could be an early sign of Reye's syndrome, a rare but serious illness.

Allergy alert:Aspirin may cause a severe allergic reaction which may include:

- hives
- facial swelling
- asthma (wheezing)
- shock

Stomach bleeding warning:

- This product contains an NSAID, which may cause severe stomach bleeding. The chance is higher if you:
- are age 60 or older
- have had stomach ulcers or bleeding problems
- take a blood thinning (anticoagulant) or steroid drug
- take other drugs containing prescription or nonprescription NSAIDs (aspirin, ibuprofen, naproxen, or others)
- have 3 or more alcoholic drinks every day while using this product
- take more or for a longer time than directed

Do not use

- if you are allergic to aspirin or any other pain reliever/fever reducer
- if you have ever had an allergic reaction to this product or any of its ingredients

Ask a doctor before use if

- stomach bleeding warning applies to you
- you have a history of stomach problems, such as heartburn
- you have high blood pressure, heart disease, liver cirrhosis or kidney disease
- you are taking a diuretic
- you have asthma

Ask a doctor or pharmacist before use if you are

taking a prescription drug for

- gout
- diabetes
- arthritis

Stop use and ask a doctor if

- an allergic reaction occurs. Seek medical help right away.
- you experience any of the following signs of stomach bleeding:
  - feel faint
  - vomit blood
  - have bloody or black stools
  - have stomach pain that does not get better
  - pain gets worse or lasts for more than 10 days
  - fever gets worse or lasts for more than 3 days
  - redness or swelling present
  - new symptoms occur
  - ringing in the ears or loss of hearing occurs

PREGNANCY OR BREAST FEEDING

If pregnant or breast-feeding, ask a health professional before use. It is especially important not to use aspirin at 20 weeks or later in pregnancy unless definitely directed to do so by a doctor because it may cause problems in the unborn child or complications during delivery.

Keep out of reach of children.

In case of overdose, get medical help or contact a Poison Control Center (1-800-222-1222) right away.

Directions

- drink a full glass of water with each dose
- adults and children 12 years and over:
  - take 4 to 8 tablets every 4 hours, not to exceed 48 tablets in 24 hours unless directed by a doctor
- children under 12 years:consult a doctor

Other information

- store at 25°C (77°F) excursions permitted between 15°-30°C (59°-68°F).
- DO NOT USE IF PRINTED SEAL UNDER CAP IS MISSING OR DAMAGED

Inactive ingredients

Starch, Povidone, Microcrystalline Cellulose, Croscarmellose Sodium, Stearic Acid, Colloidal Silicon Dioxide, Methacrylic Acid and Ethyl acrylate Co-polymer, Triethyl Citrate, Talc, Fumed Silica, Titanium Dioxide, D&C Yellow #10, FD&C Yellow #6.

Questions or comments?

call toll-free 1-844-912-4012

Distributed by:

Twin Med LLC

Santa Fe Springs,

CA 90670

www.procureproducts.com

Made in the USA

PRINCIPAL DISPLAY PANEL

NDC 55681-403-03

*Compare to active ingredients in Bayer®Aspirin Low Dose 81 mg

Adult Low Dose Pain Reliever Aspirin Delayed Release Tablets, 81 mg

Pain Reliever (NSAID)

Enteric Coated

300 Tablets

*This product is not manufactured or distributed by the owner of the registered trademark Bayer®.